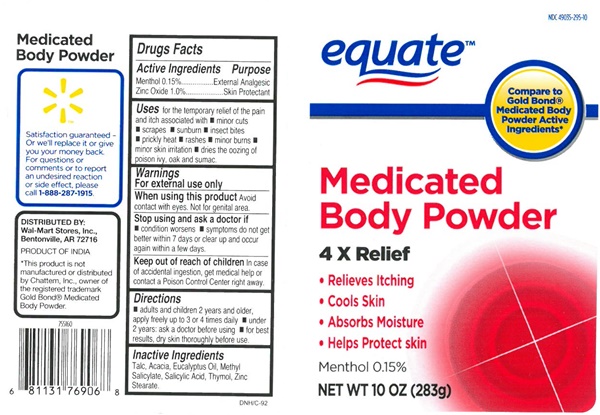 DRUG LABEL: Medicated Body
NDC: 49035-295 | Form: POWDER
Manufacturer: Walmart Stores Inc
Category: otc | Type: HUMAN OTC DRUG LABEL
Date: 20161218

ACTIVE INGREDIENTS: MENTHOL 3 mg/2 g; ZINC OXIDE 20 mg/2 g
INACTIVE INGREDIENTS: TALC; ACACIA; EUCALYPTUS OIL; MENTHYL SALICYLATE, (+/-)-; SALICYLIC ACID; THYMOL; ZINC STEARATE

Medicated Body Powder - 295

Drug Facts Active Ingredients

Menthol 0.15 %

Zinc Oxide 1.0%

Purpose

External Analgesic

Skin Protectant

Uses

for the temporary relief of the pain and itch associated with

- minor cuts
- scrapes
- sunburn
- insect bites
- prickly heat
- rashes
- minor burns
- minor skin irritations
- dries the oozing of poison ivy, oak and sumac.

Keep out of reach of children. In case of accidential ingestion, get medical help or contact a Poison Control Center right away.

Warnings

For external use only

When usin this product

Avoid contact with eyes. Not for genital area.

Stop use and ask a doctor if

- condition worsens
- symptoms do not get better within 7 days or clear up and occur again within a few days

Directions

- adults and children 2 years and older, apply freely up to 3 or 4 times daily
- under 2 years: ask a doctor before using
- for best results, dry skin thoroughly before use

Inactive Ingredients

Talc, Acacia, Eucalyputus Oil, Menthyl Salicylate, Salicylic Acid, Thymol, Zinc Stearate

equate Medicated Body Powder product label

NDC 49035-295-10

equate™

Compare to GoldBond® Medicated Body Powder Active Ingredients

Medicated Body Powder

4 X Relief

- Relieves Itcing
- Cools Skin
- Absorbs Moisture
- Helps Protect skin

Menthol 0.15%

NET WT 10 OZ (283g)

Medicated Body Powder

Satisfaction guarenteed- or we'll replace it or give you your money back.

For questions or comments or to report an undesired reaction or side effect, please call 1-888-287-1915

DISTRIBUTED BY:
Wal-Mart Stores, Inc.,

Bentonville, AR 72716

PRODUCT OF IINDIA

*This product is not manufactured or distributed by Chattem, Inc., owner of the registered trademark Gold Bond® Medicated body Powder.

DNH/C-92